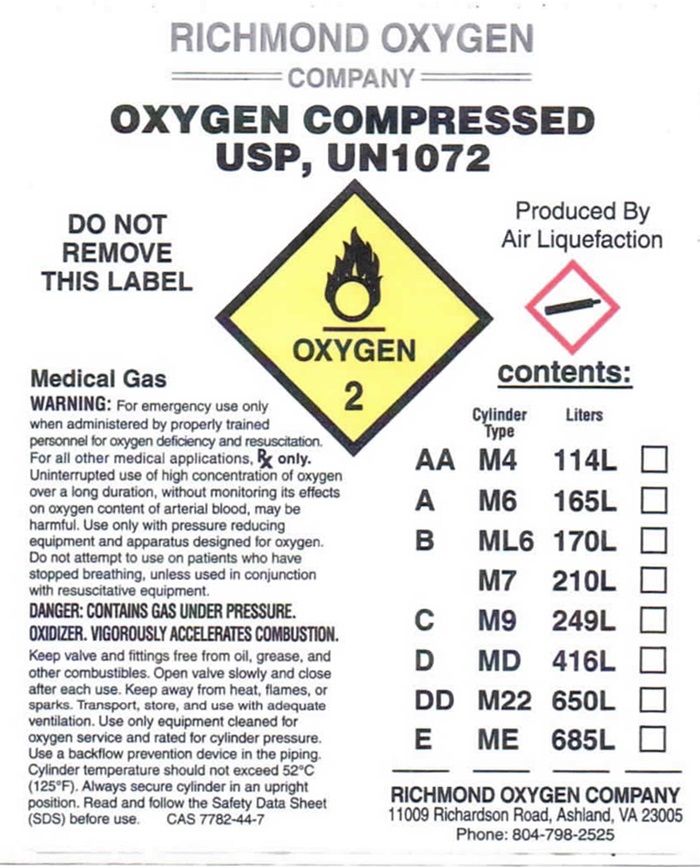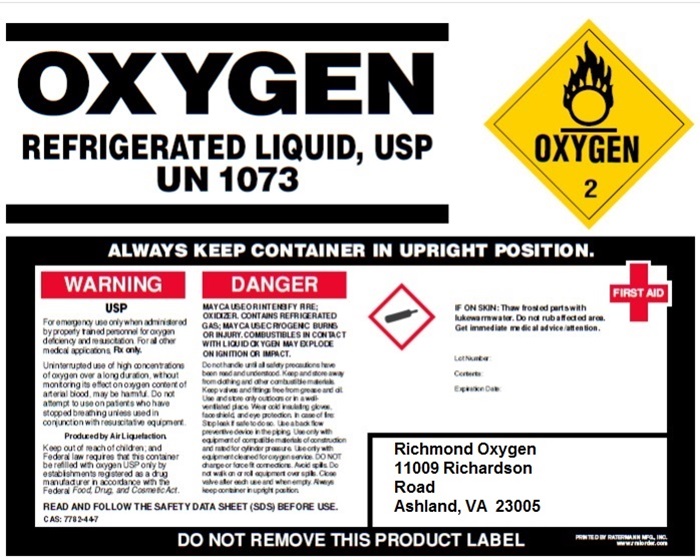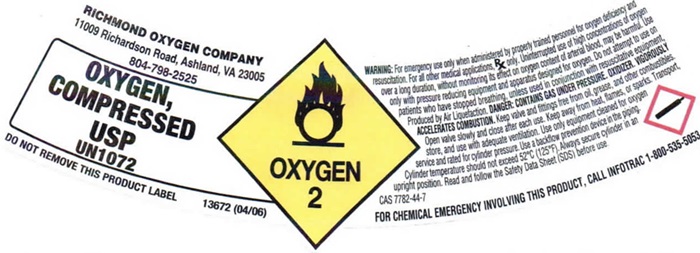 DRUG LABEL: Oxygen
NDC: 59534-001 | Form: GAS
Manufacturer: Richmond Oxygen Company Inc.
Category: prescription | Type: HUMAN PRESCRIPTION DRUG LABEL
Date: 20241028

ACTIVE INGREDIENTS: Oxygen 99 L/100 L

Oxygen

Oxygen Shoulder label

RICHMOND OXYGEN COMPNAY

11009 Richardson Road, Ashland, VA 23005

804-798-2525

OXYGEN, COMPRESSED USP UN 1072 OXYGEN 2 DO NOT REMOVE THIS PRODUCT LABEL. 13672 (04/06)

WARNING: For emergency use only when administered by properly trained personnel for oxygen deficiency and resuscitation. For all other medical applications, Rx only. Uninterrupted use of high concentrations of oxygen over a long duration, without monitoring its effect on oxygen content of arterial blood, may be harmful. Do not attempt to use on patients who have stopped breathing unless used in conjunction with resuscitative equipment. Produced by Air Liquefaction. DANGER: CONTAINS GAS UNDER PRESSURE. OXIDIZER. VIGOROUSLY ACCELERATES COMBUTSION.

Keep valves and fittings free from grease and other combustibles. Open valve slowly and close after each use. Keep away from heat., fumes or sparks. Transport, store, and use with adequate ventilation. Use only equipment cleaned for oxygen service and rated for cylinder pressure. Use a backflow prevention device in the piping. Cylinder temperature should not exceed 52°C (125° F). Always secure cylinder in an upright position. Read and follow the Safety Data Sheet (SDS) before use. CAS 7782-44-7

FOR CHEMICAL EMERGENCY INVOLVING THIS PRODUCT, CALL INFOTRAC 1-800-535-5053

Oxygen Body Label

RICHMOND OXYGEN

COMPANY

OXYGEN, COMPRESSED USP, UN1072 OXYGEN 2

DO NOT REMOVE THIS LABEL OXYGEN 2 PRODUCED BY AIR LIQUEFACTION

Medical Gas

WARNING: For emergency use only when administered by properly trained personnel for oxygen deficiency and resuscitation. For all other medical applications. Rx only. Uninterrupted use of high concentrations of oxygen over a long duration without monitoring its effect on oxygen content of arterial blood, may be harmful. Use only with pressure reducing equipment and apparatus designed for oxygen. Do not attempt to use on patient’s ho have stopped breathing, unless use in conjunction with resuscitative equipment.

DANGER: CONTAINS GAS UNDER PRESSURE. OXIDIZER. VIGOROUSLY ACCELERATES COMBUSTION.

Keep valves and fittings free from grease and other combustibles. Open valve slowly and close valve after each use. Keep away from heat, flames, or sparks. Transport, store, and use with adequate ventilation. Use only equipment cleaned for oxygen service and rated for cylinder pressure. Use a backflow preventive device in the piping. Cylinder temperature should not exceed 52° C (125° F). Read and follow the Safety Data Sheet (SDS) before use. CAS 7782-44-7

Contents:

Cylinder type Liters

AA M4 114L _____

A M6 165L _____

B ML6 170L _____

M7 210L _____

C M9 249L _____

D MD 416L _____

DD M22 650L _____

E ME 685L _____

__ ____ ____ _____

RICHMOND OXYGEN COMPANY

11009 Richardson Road, Ashland, VA 23005

Phone: 804-798-2525

Oxygen Refrigerated

OXYGEN, REFRIGERATED LIQUID, USP UN1073

OXYGEN 2

ALWAYS KEEP CONTAINER IN UPRIGHT POSITION.

WARNING USP

For emergency use only when administered by properly trained personnel for oxygen deficiency and resuscitation. For all other medical applications, Rx only.

Uninterrupted use of high concentrations of oxygen over a long duration, without monitoring its effect on oxygen content of arterial blood, may be harmful. Do not attempt to use on patients who have stopped breathing unless used in conjunction of resuscitative equipment.

Produced by Air Liquefaction.

Keep out of reach of children; and Federal law requires that this container be refilled with oxygen USP only by establishments registered as a drug manufacturer in accordance with the Federal Food, Drug, and Cosmetic Act.

DANGER:

MAY CAUSE OR INTENSIFY FIRE; OXIDER, CONTAINS REFRIGERATED GAS; MAY CAUSE CRYOGENIC BURNS OR INJURY. COMBUSTIBELS IN CONTACT WITH LIQUID OXYGEN MAY EXPLODE ON IGNITION OR IMPACT.

Do not handle until all safety precautions have been read and understood. Keep and store away from clothing and other combustible materials. Keep valves and fittings free from grease and oil. Use and store only outdoors or in a well-ventilated place. Wear cold insulating gloves, face shield, and eye protection. In case of fire: Stop leak if safe to do so. Use a backflow preventive device in the piping. Use only the equipment of compatible materials equipment cleaned for oxygen service. DO NOT change or force fit connections. Avoid spills. Do not walk on or roll equipment over spills. Close valve after each use and when empty. Always keep container in upright position.

READ AND FOLLOW THE SAFETY DATA SHEET (SDS) BEFORE USE. CAS: 7782-44-7

FIRST AID FIRST AID: IF ON SKIN: Thaw affected parts with lukewarm water. Do not rub affected area. Get immediate medical advice/attention.

Lot Number:

Contents:

Expiration Date:

Richmond Oxygen

11009 Richardson Road

Ashland, VA 23005

DO NOT REMOVE THIS PRODUCT LABEL